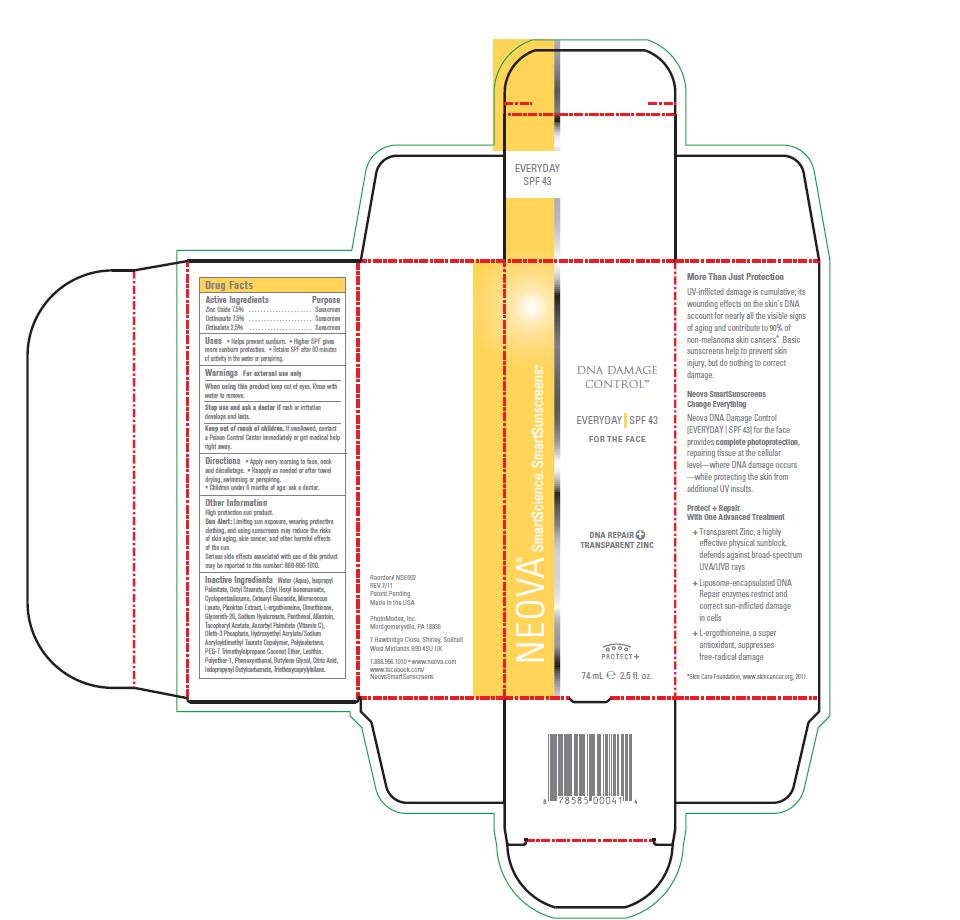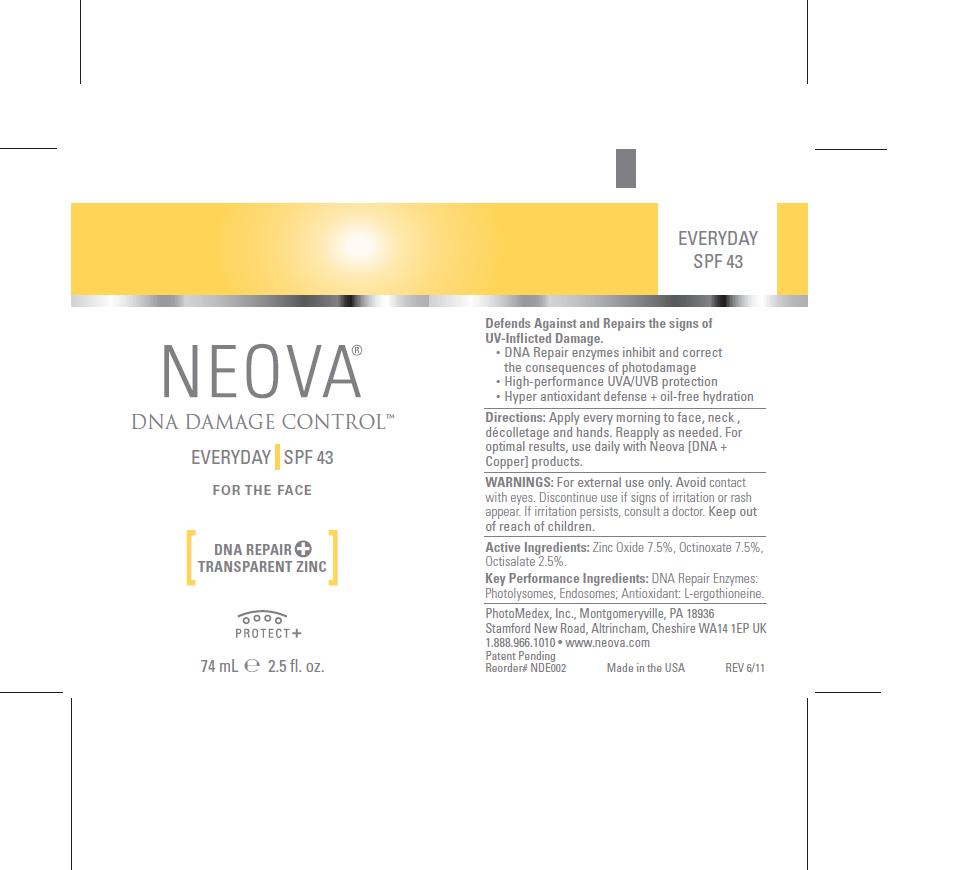 DRUG LABEL: Neova DNA Damage Control - Everyday
NDC: 62362-139 | Form: EMULSION
Manufacturer: PhotoMedex, Inc.
Category: otc | Type: HUMAN OTC DRUG LABEL
Date: 20120106

ACTIVE INGREDIENTS: Zinc Oxide 7.5 mL/100 mL; Octinoxate 7.5 mL/100 mL; Octisalate 2.5 mL/100 mL
INACTIVE INGREDIENTS: Water; Isopropyl Palmitate; Octyl Stearate; Ethylhexyl Isononanoate; Cyclomethicone 5  ; Cetearyl Glucoside; Ergothioneine; Dimethicone; Glycereth-26; Hyaluronate Sodium; Panthenol; Allantoin; Alpha-Tocopherol Acetate; Ascorbyl Palmitate; Oleth-3 Phosphate; Polyisobutylene (1300 MW); Phenoxyethanol; Butylene Glycol; Citric Acid; Iodopropynyl Butylcarbamate; Triethoxycaprylylsilane

Neova DNA Damage Control - Everyday SPF 43 - Drug Facts

Active Ingredients

Zinc Oxide 7.5%, Octinoxate 7.5%, Octisalate 2.5%

PURPOSE

Sunscreen

INDICATIONS AND USAGE

• Helps prevent sunburn. • Higher SPF gives
more sunburn protection. • Retains SPF after 80 minutes
of activity in the water or perspiring.

Warnings

- For external use only.
- When using this product keep out of eyes. Rinse with water to remove.
- Stop use and ask a doctor if rash or irritation develops and lasts.
- Keep out of reach of children. If swallowed, contact a Poison Control Center immediately or get medical help right away.

When using this product

Keep out of eyes. Rinse with water to remove.

Stop use and ask a doctor if

Rash or irritation develops and lasts.

Keep out of reach of children

If swallowed, contact a Poison Control Center immediately or get medical help right away.

Directions

• Apply every morning to face, neck
and décolletage. • Reapply as needed or after towel
drying, swimming or perspiring.
• Children under 6 months of age: ask a doctor.

Other Information

High protection sun product.
Sun Alert: Limiting sun exposure, wearing protective
clothing, and using sunscreens may reduce the risks
of skin aging, skin cancer, and other harmful effects
of the sun.
Serious side effects associated with use of this product
may be reported to this number: 888-966-1010.

Inactive Ingredients

Water (Aqua), Isopropyl
Palmitate, Octyl Stearate, Ethyl Hexyl Isononanoate,
Cyclopentasiloxane, Cetearyl Glucoside, Micrococcus
Lysate, Plankton Extract, L-ergothioneine, Dimethicone,
Glycereth-26, Sodium Hyaluronate, Panthenol, Allantoin,
Tocopheryl Acetate, Ascorbyl Palmitate (Vitamin C),
Oleth-3 Phosphate, Hydroxyethyl Acrylate/Sodium
Acryloyldimethyl Taurate Copolymer, Polyisobutene,
PEG-7 Trimethylolpropane Coconut Ether, Lecithin,
Polyether-1, Phenoxyethanol, Butylene Glycol, Citric Acid,
Iodopropynyl Butylcarbamate, Triethoxycaprylylsilane.

Image of box and label

DNADamageControlEday.jpg DNADConEDAYBox.jpg